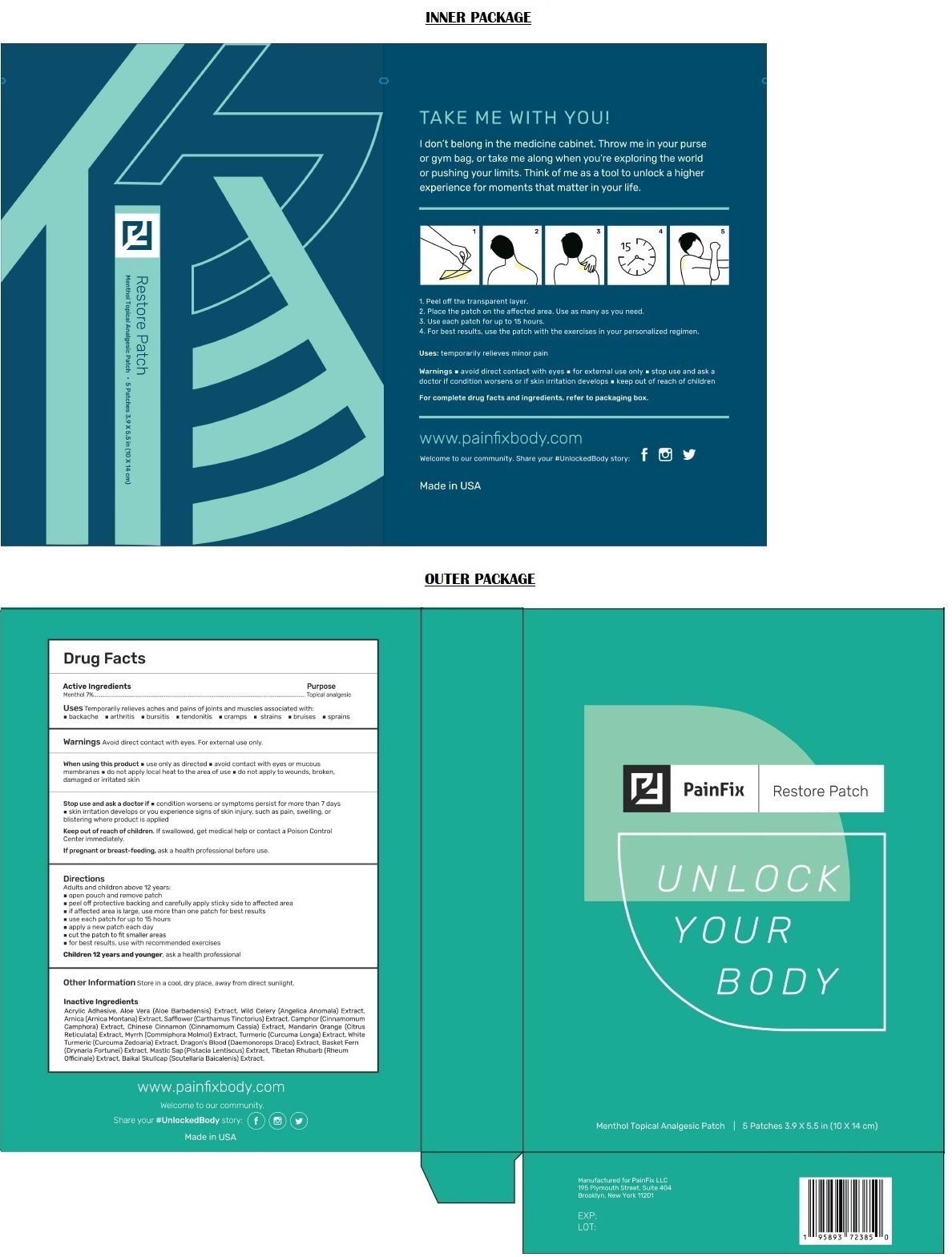 DRUG LABEL: PainFix Restore
NDC: 72749-008 | Form: PATCH
Manufacturer: PainFix LLC
Category: otc | Type: HUMAN OTC DRUG LABEL
Date: 20211220

ACTIVE INGREDIENTS: MENTHOL, UNSPECIFIED FORM 70 mg/1 g
INACTIVE INGREDIENTS: ALOE VERA LEAF; ANGELICA ANOMALA ROOT; ARNICA MONTANA WHOLE; CARTHAMUS TINCTORIUS FLOWER BUD; CINNAMOMUM CAMPHORA RESIN; CHINESE CINNAMON; CITRUS RETICULATA WHOLE; MYRRH; TURMERIC; CURCUMA ZEDOARIA ROOT; DRAGON'S BLOOD; DRYNARIA FORTUNEI ROOT; PISTACIA LENTISCUS RESIN OIL; RHEUM OFFICINALE ROOT; SCUTELLARIA BAICALENSIS ROOT

PainFix Restore Patch

Active Ingredients

Menthol 7%

Purpose

Topical analgesic

Uses

Temporarily relieves aches and pains of joints and muscles associated with: • backache • arthritis • bursitis • tendonitis • cramps • strains • bruises • sprains

Warnings

Avoid direct contact with eyes. For external use only.

When using this product • use only as directed • avoid contact with eyes or mucous membranes • do not apply local heat to the area of use • do not apply to wounds, broken, damaged or irritated skin

Stop use and ask a doctor if • condition worsens or symptoms persist for more than 7 days • skin irritation develops or you experience signs of skin injury, such as pain, swelling, or blistering where product is applied

If pregnant or breast-feeding, ask a health professional before use.

Keep out of reach of children. If swallowed, get medical help or contact a Poison Control Center immediately.

Directions

Adults and children above 12 years:
• open pouch and remove patch
• peel off protective backing and carefully apply sticky side to affected area
• if affected area is large, use more than one patch for best results
• use each patch for up to 15 hours
• apply a new patch each day
• cut the patch to fit smaller areas
• for best results, use with recommended exercises

Children 12 years and younger, ask a health professional

Other Information

Store in a cool, dry place, away from direct sunlight.

Inactive Ingredients

Acrylic Adhesive, Aloe Vera (Aloe Barbadensis) Extract, Wild Celery (Angelica Anomala) Extract, Arnica (Arnica Montana) Extract, Safflower (Carthamus Tinctorius) Extract, Camphor (Cinnamomum Camphora) Extract, Chinese Cinnamon (Cinnamomum Cassia) Extract, Mandarin Orange (Citrus Reticulata) Extract, Myrrh (Commiphora Molmol) Extract, Turmeric (Curcuma Longa) Extract, White Turmeric (Curcuma zedoaria) Extract, Dragon's Blood (Daemonorops Draco) Extract, Basket Fern (Drynaria Fortunei) Extract, Mastic Sap (Pistacia Lentiscus) Extract, Tibetan Rhubarb (Rheum Officinale) Extract, Baikal Skullcap (Scutellaria Baicalensis) Extract.

UNLOCK YOUR BODY

TAKE ME WITH YOU!

I don't belong in the medicine cabinet. Throw me in your purse or gym bag, or take me along when you're exploring the world or pushing your limits. Think of me as a tool to unlock a higher experience for moments that matter in your life.

1. Peel off the transparent layer
2. Place the patch on the affected area. Use as many as you need.
3. Use each patch for up to 15 hours.
4. For best results, use the patch with the exercises in your personalized regimen.

www.painfixbody.com

Welcome to our community.

Share your #UnlockedBody Story:

Made in USA

Manufactured for PainFix LLC
195 Plymouth Street, Suite 404
Brooklyn, New York 11201